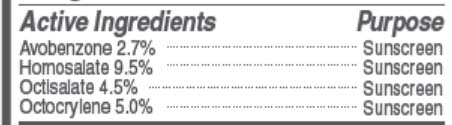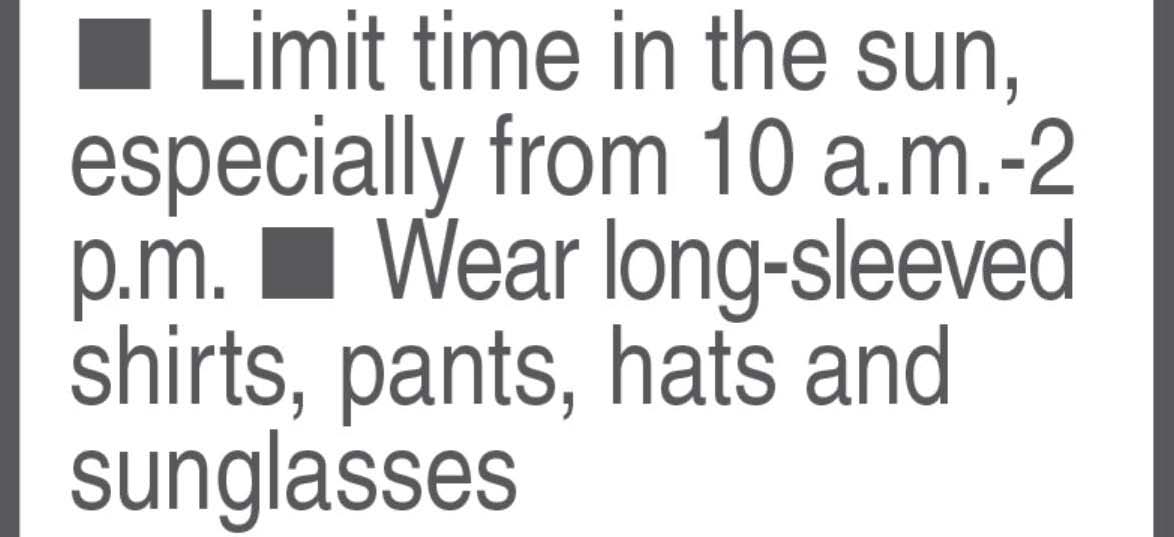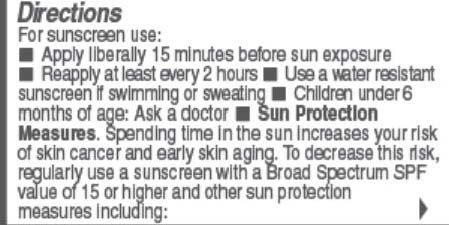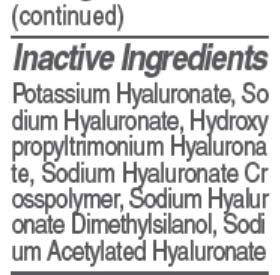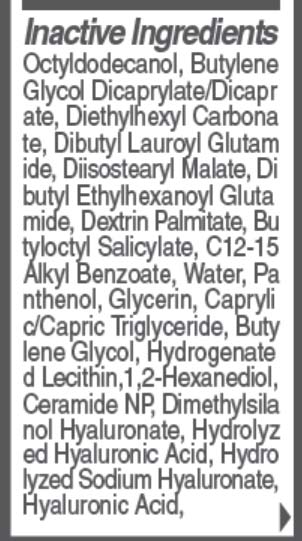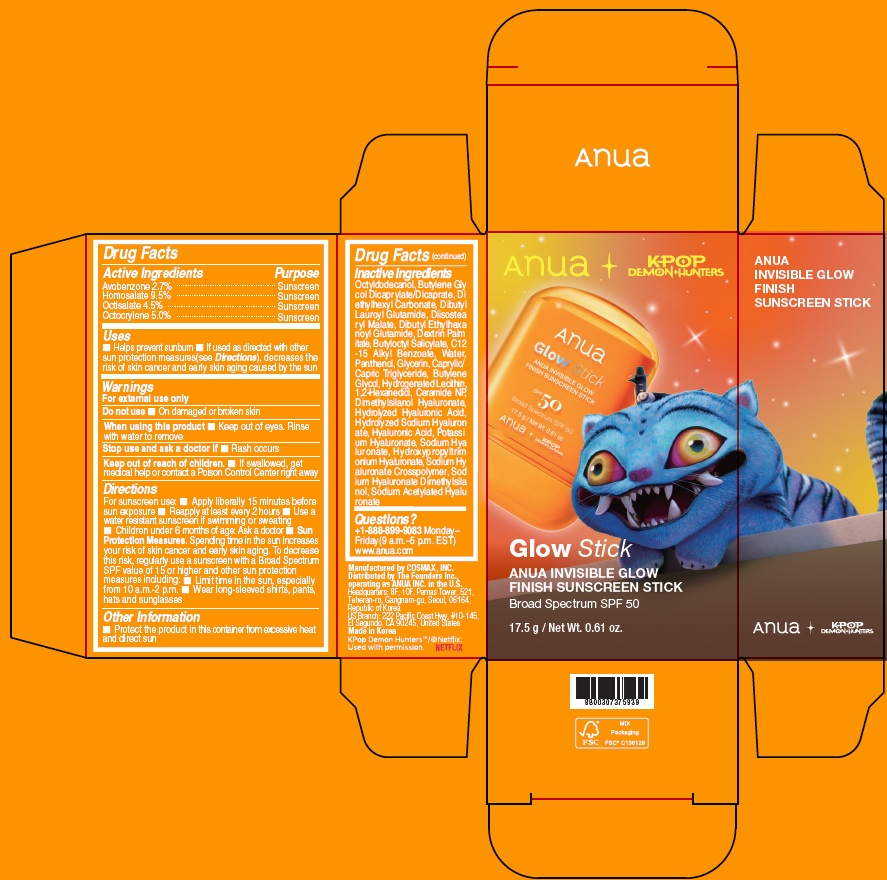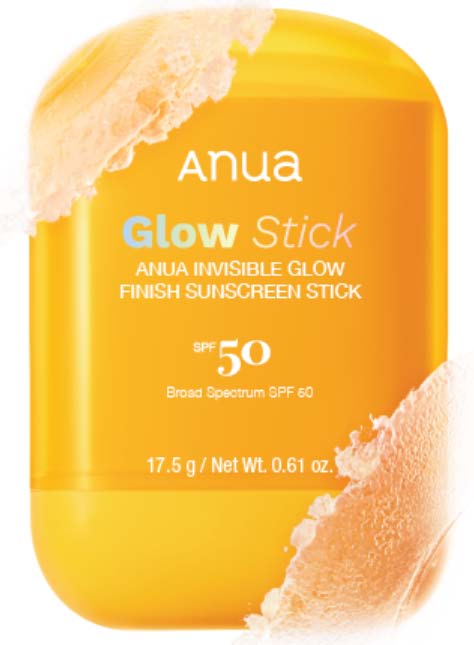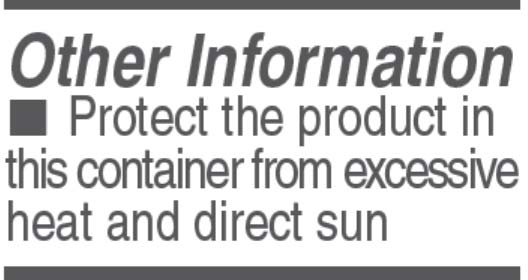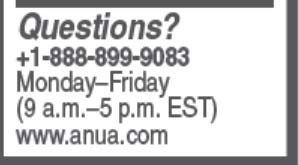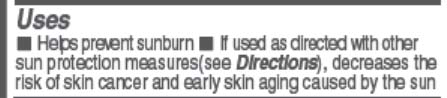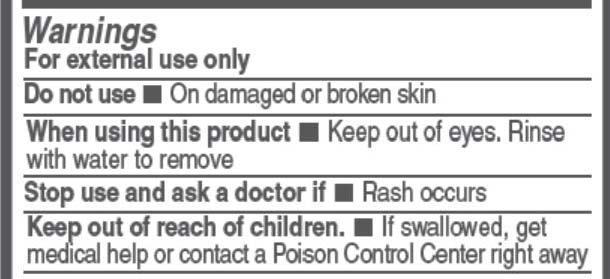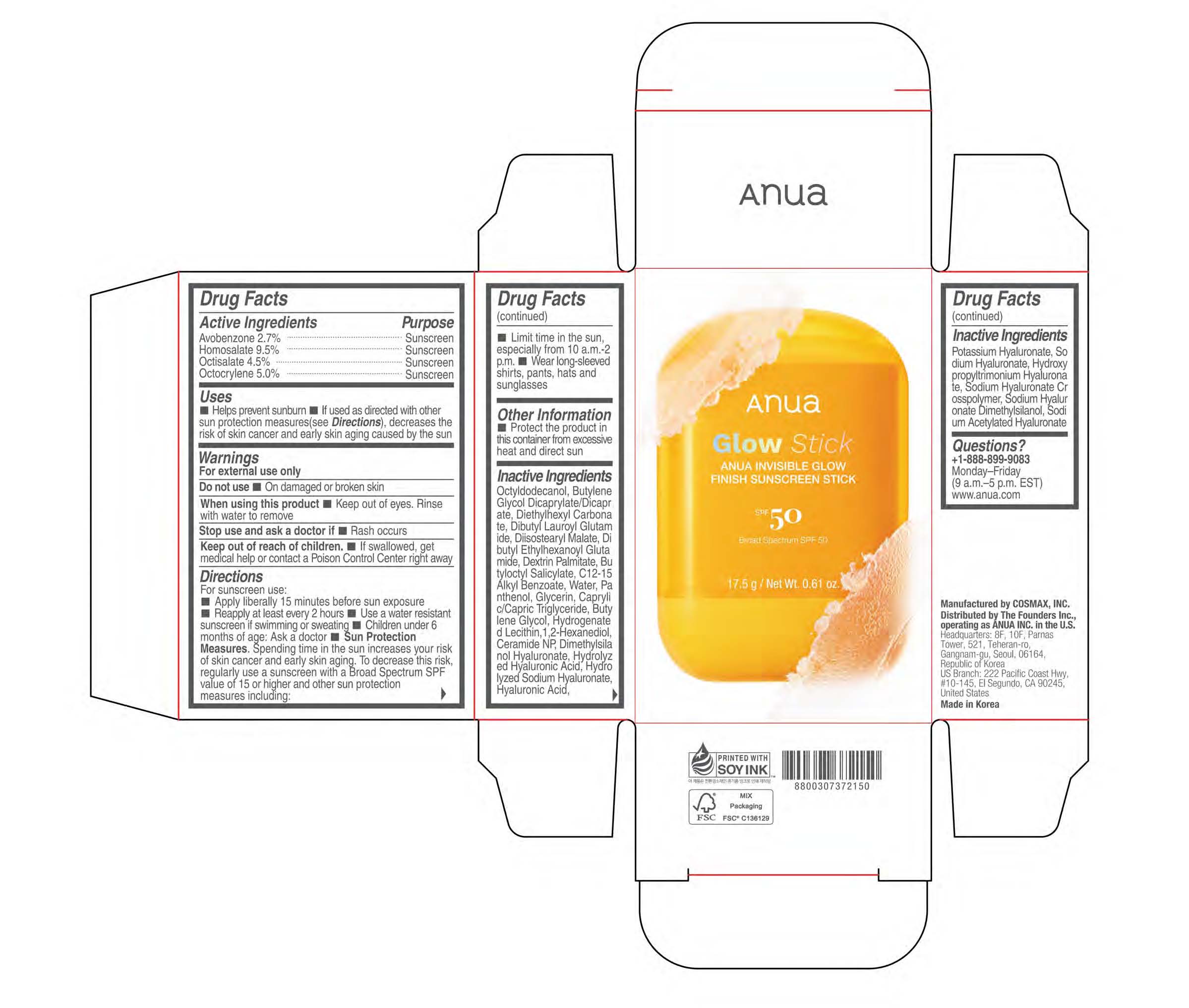 DRUG LABEL: ANUA INVISIBLE GLOW FINISH SUNSCREEN
NDC: 84610-300 | Form: STICK
Manufacturer: The Founders Inc.
Category: otc | Type: HUMAN OTC DRUG LABEL
Date: 20260119

ACTIVE INGREDIENTS: OCTOCRYLENE 5 g/100 g; AVOBENZONE 2.7 g/100 g; OCTISALATE 4.5 g/100 g; HOMOSALATE 9.5 g/100 g
INACTIVE INGREDIENTS: SODIUM ACETYLATED HYALURONATE; SODIUM HYALURONATE; BUTYLENE GLYCOL DICAPRYLATE/DICAPRATE; DIETHYLHEXYL CARBONATE; DIBUTYL LAUROYL GLUTAMIDE; WATER; DIBUTYL ETHYLHEXANOYL GLUTAMIDE; BUTYLOCTYL SALICYLATE; DIISOSTEARYL MALATE; DIMETHYLSILANOL HYALURONATE; C12-15 ALKYL BENZOATE; 1,2-HEXANEDIOL; CERAMIDE NP; OCTYLDODECANOL; PANTHENOL; GLYCERIN; CAPRYLIC/CAPRIC TRIGLYCERIDE; BUTYLENE GLYCOL; HYALURONIC ACID

ANUA INVISIBLE GLOW FINISH SUNSCREEN STICK SPF 50

Drug Facts

Warnings

Keep out of reach of children

- If swallowed, get medical help or contact a Poison Control Center right away

Do not use

- on damaged or broken skin

Stop use and ask a doctor if

- rash occurs

When using this product

- Keep out of eyes. Rinse with water to remove